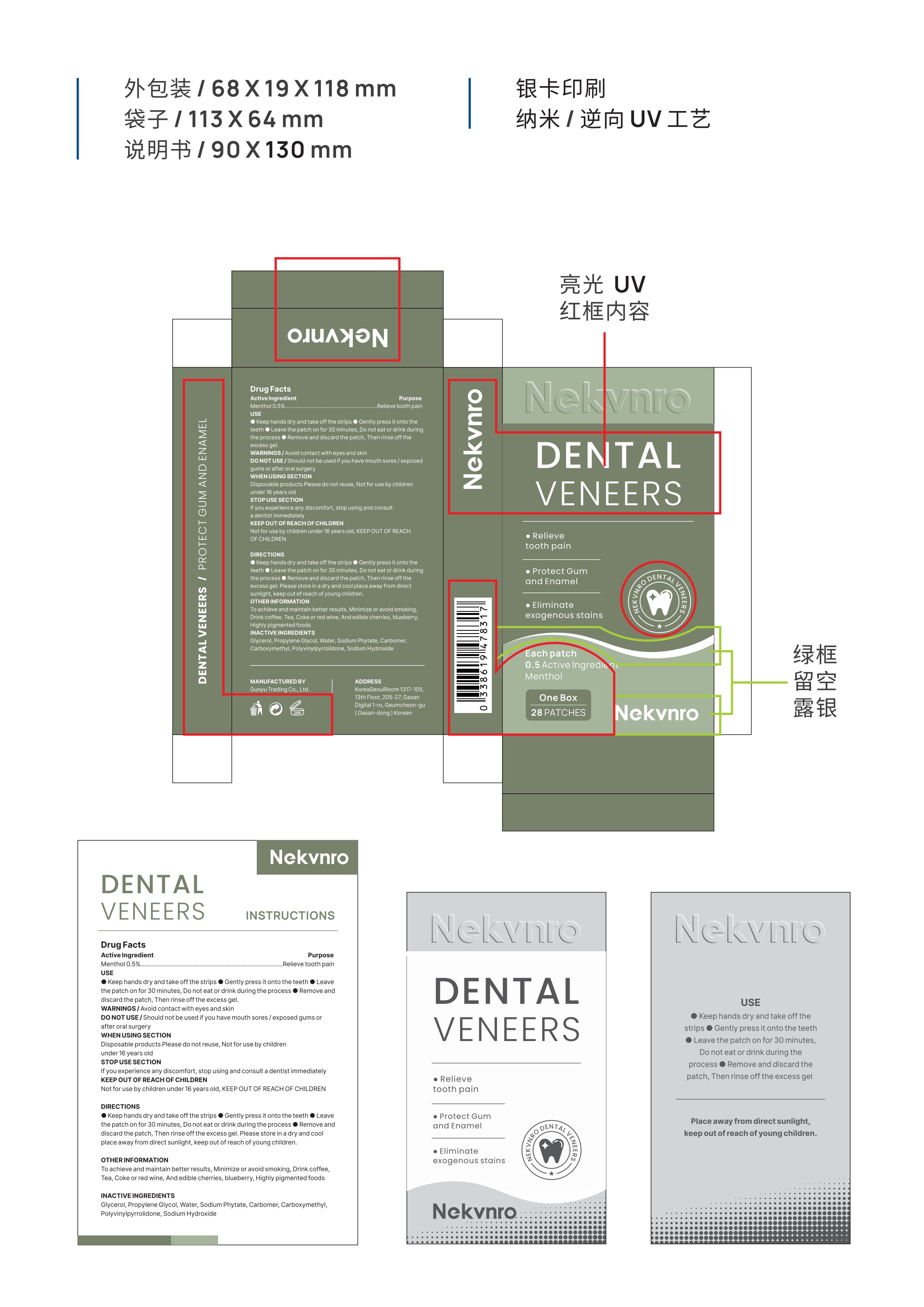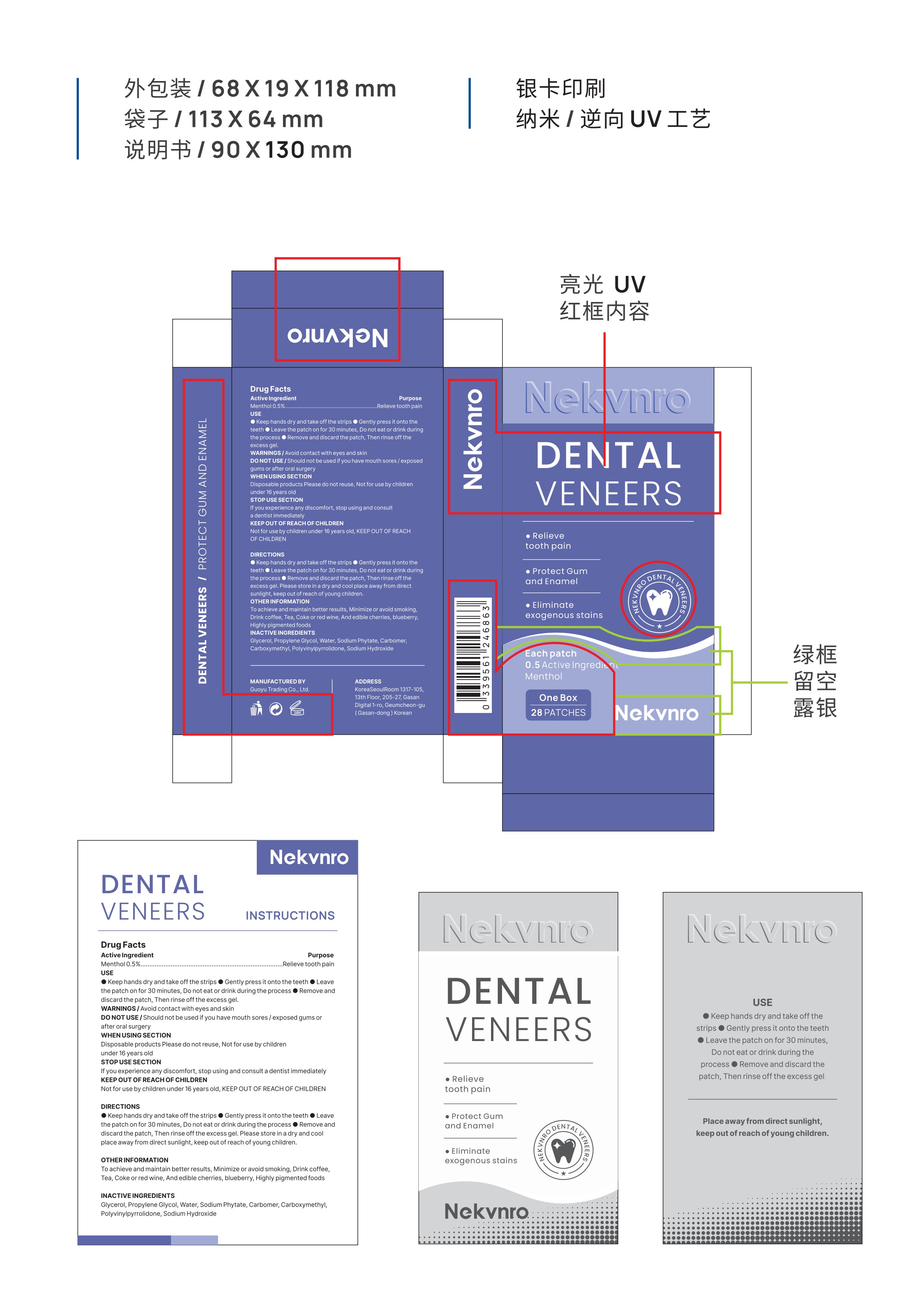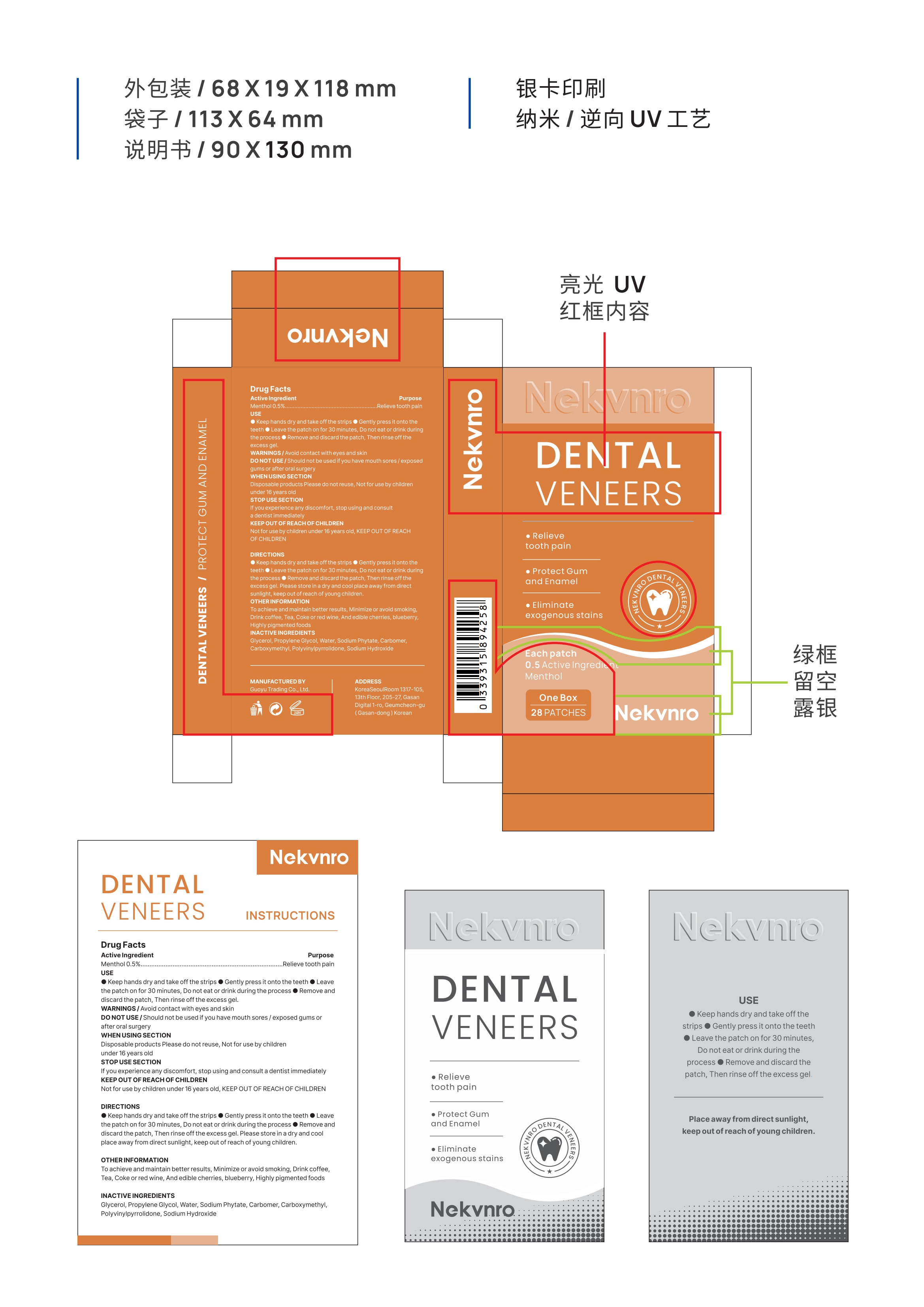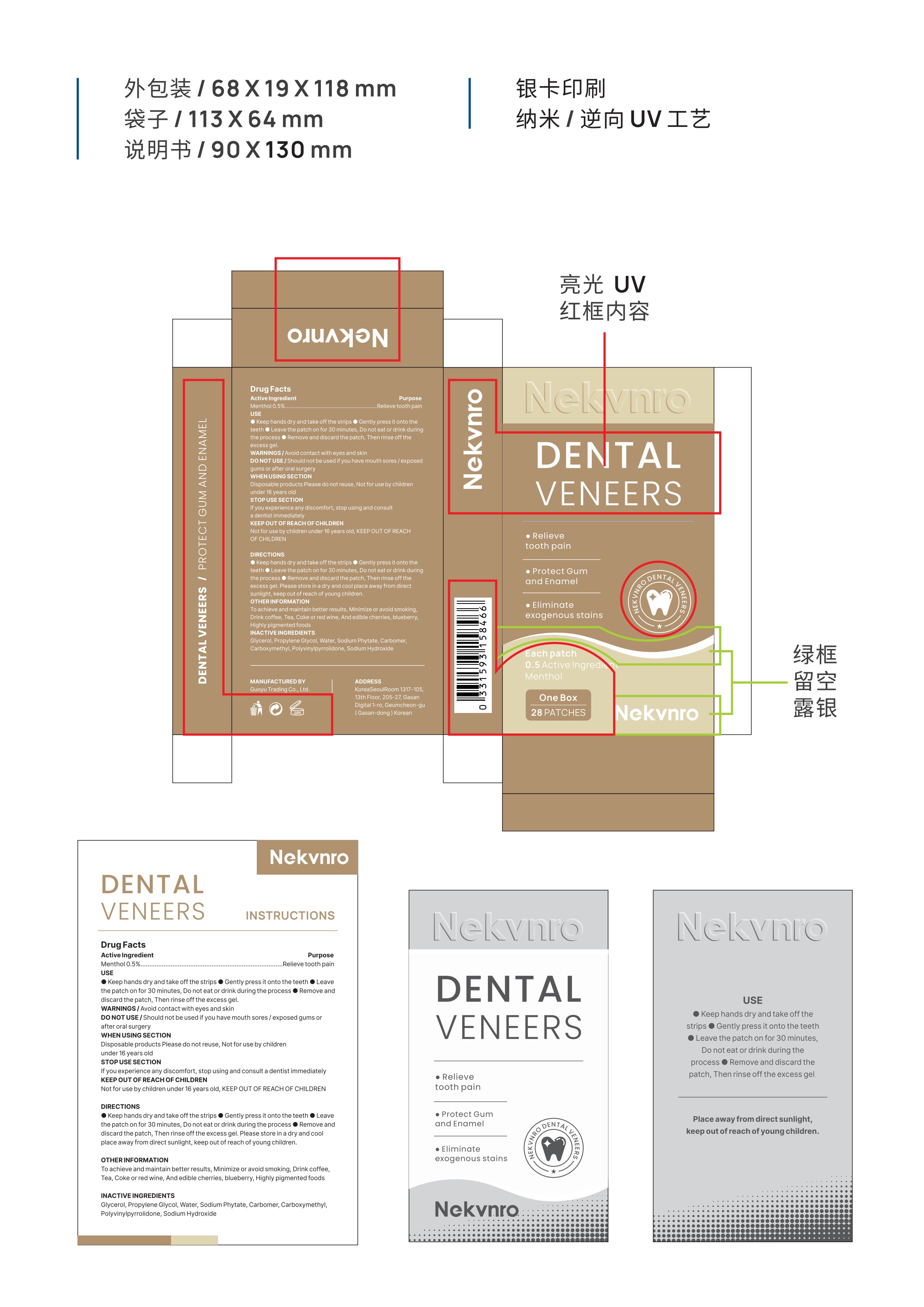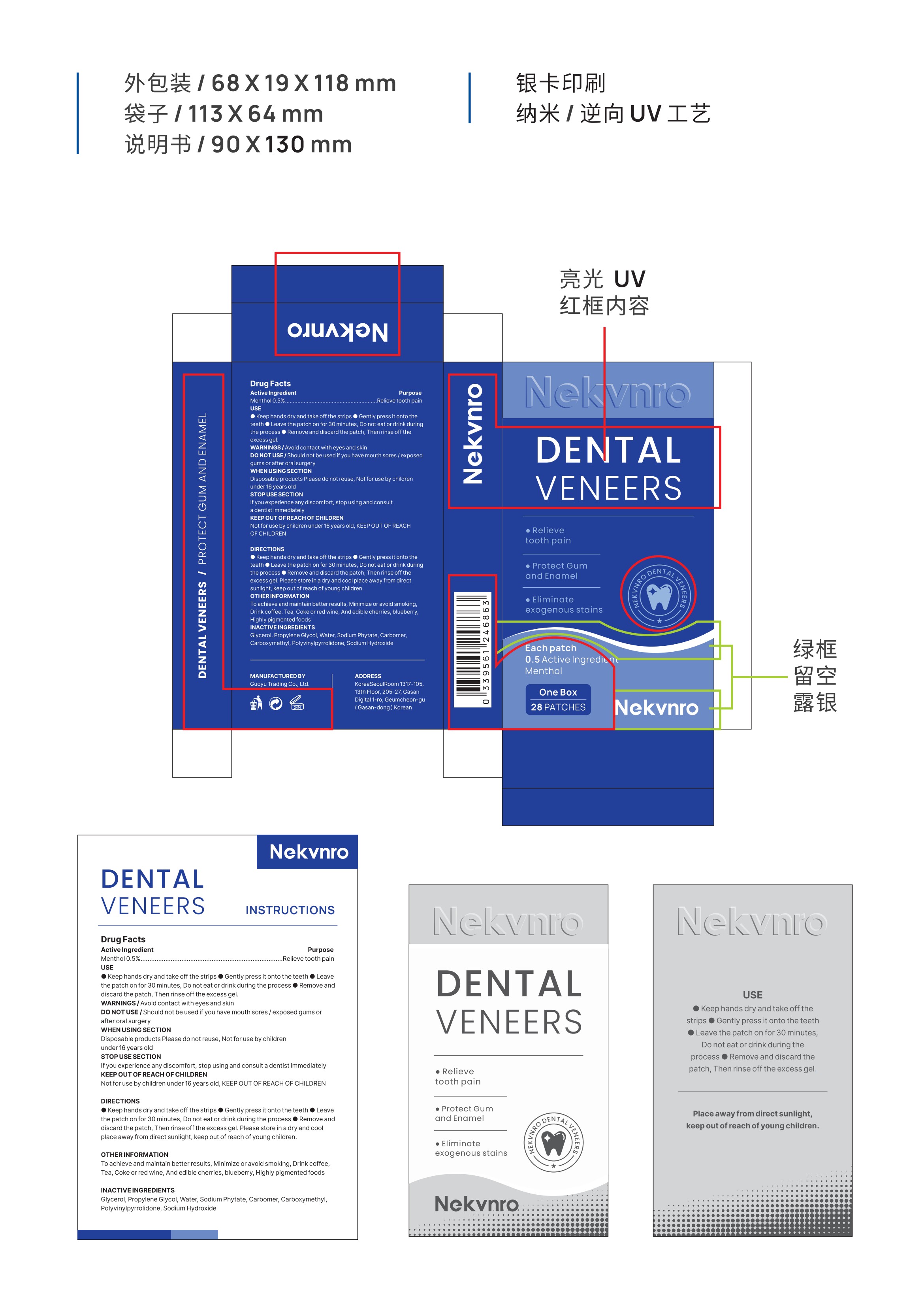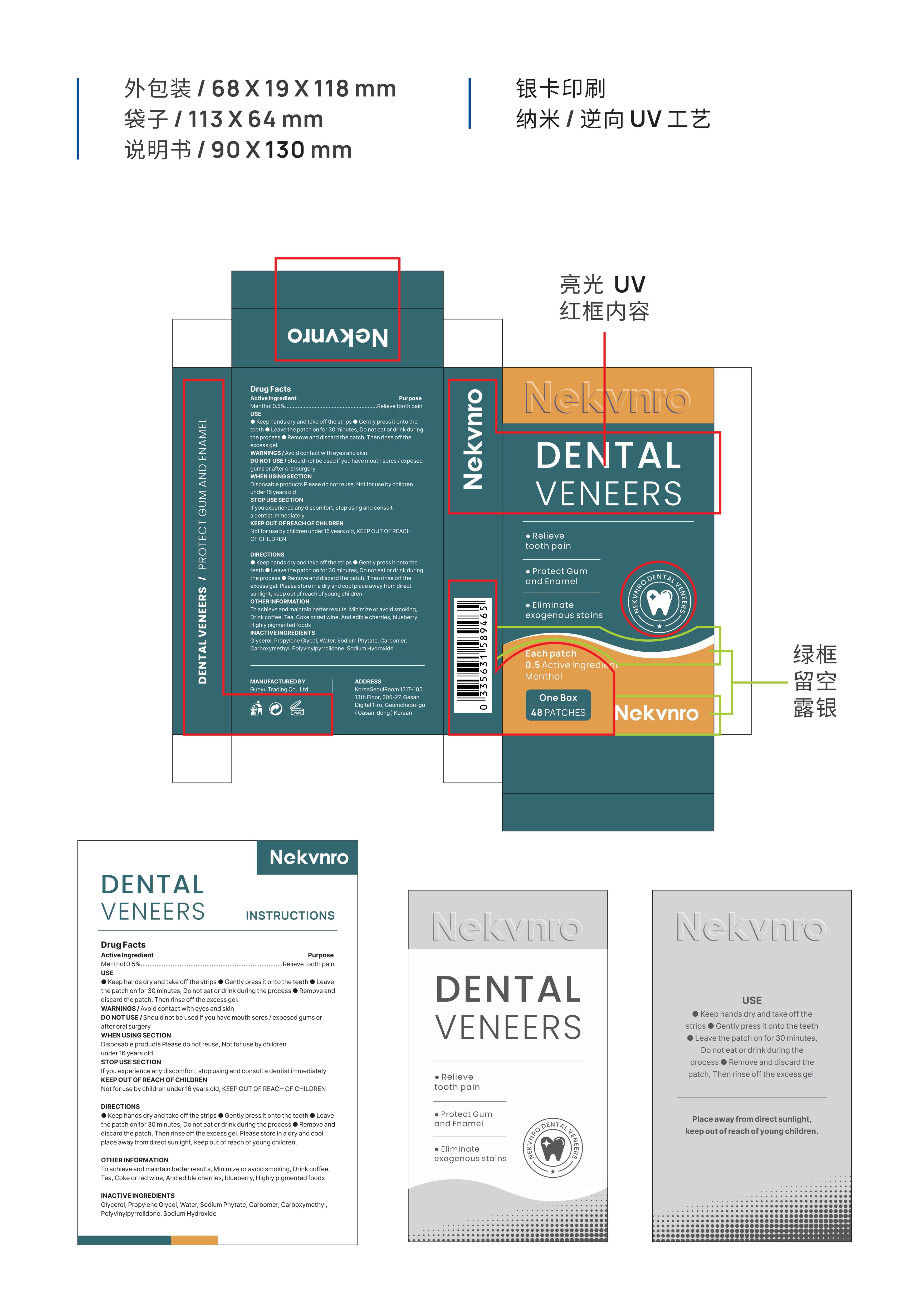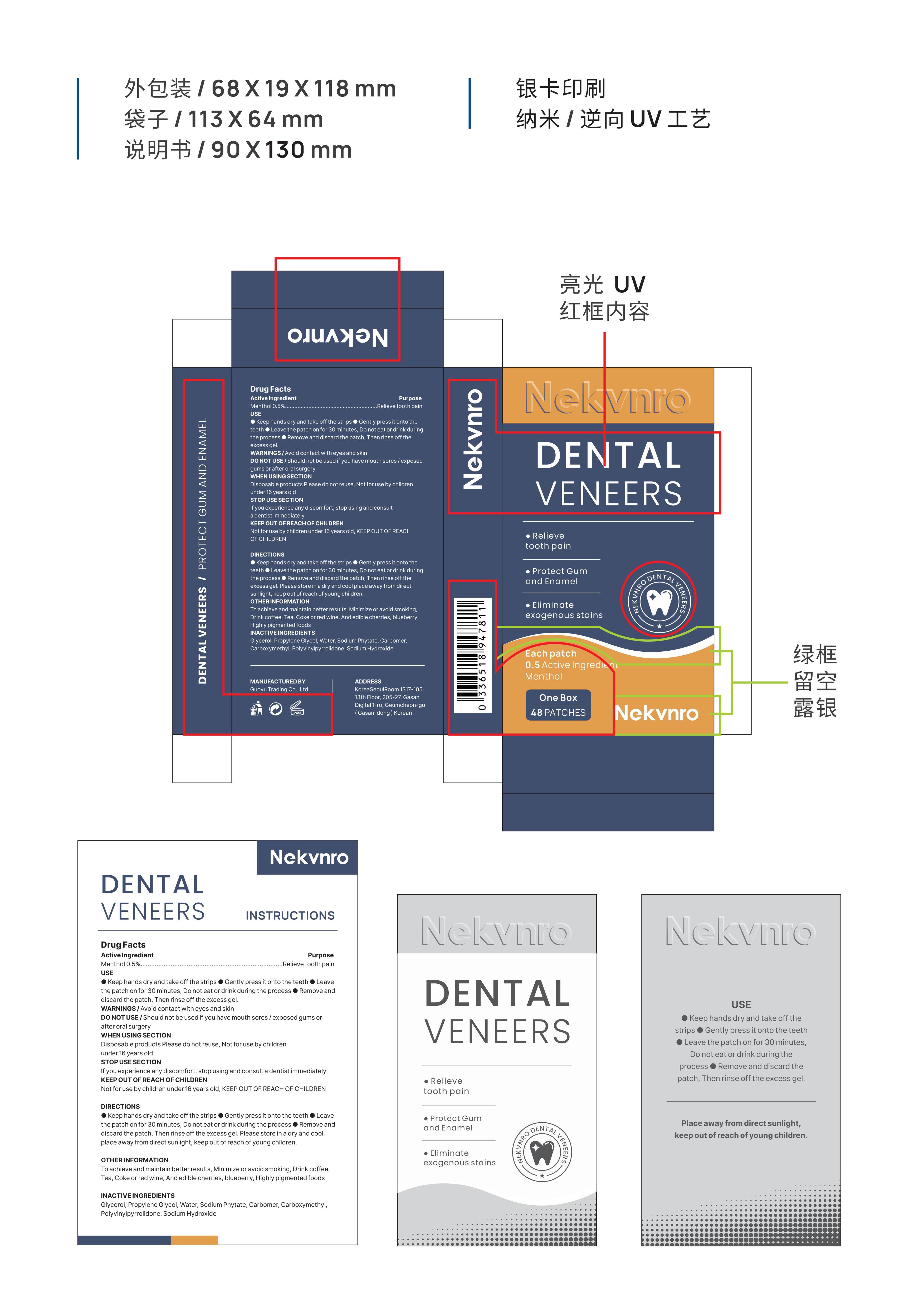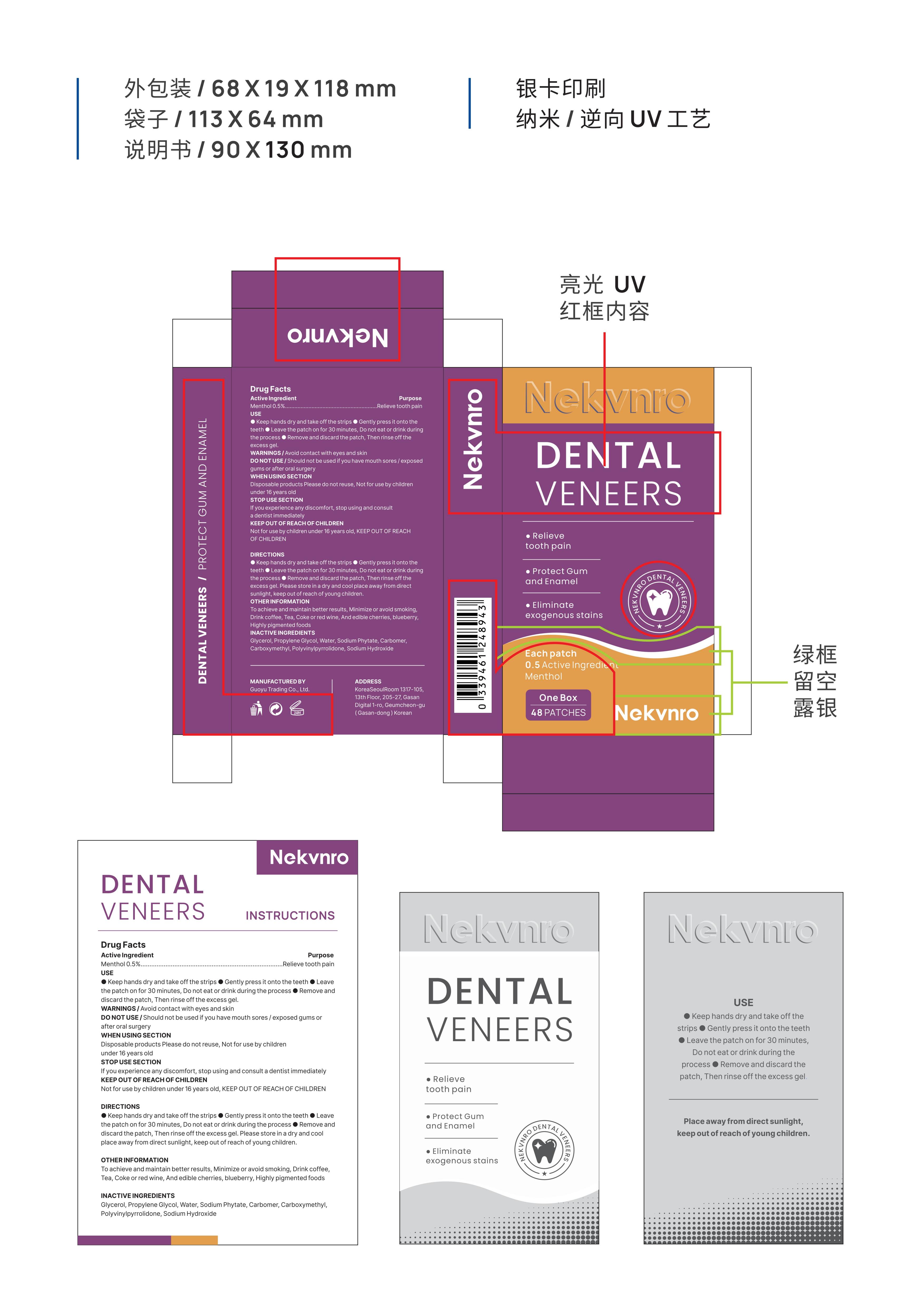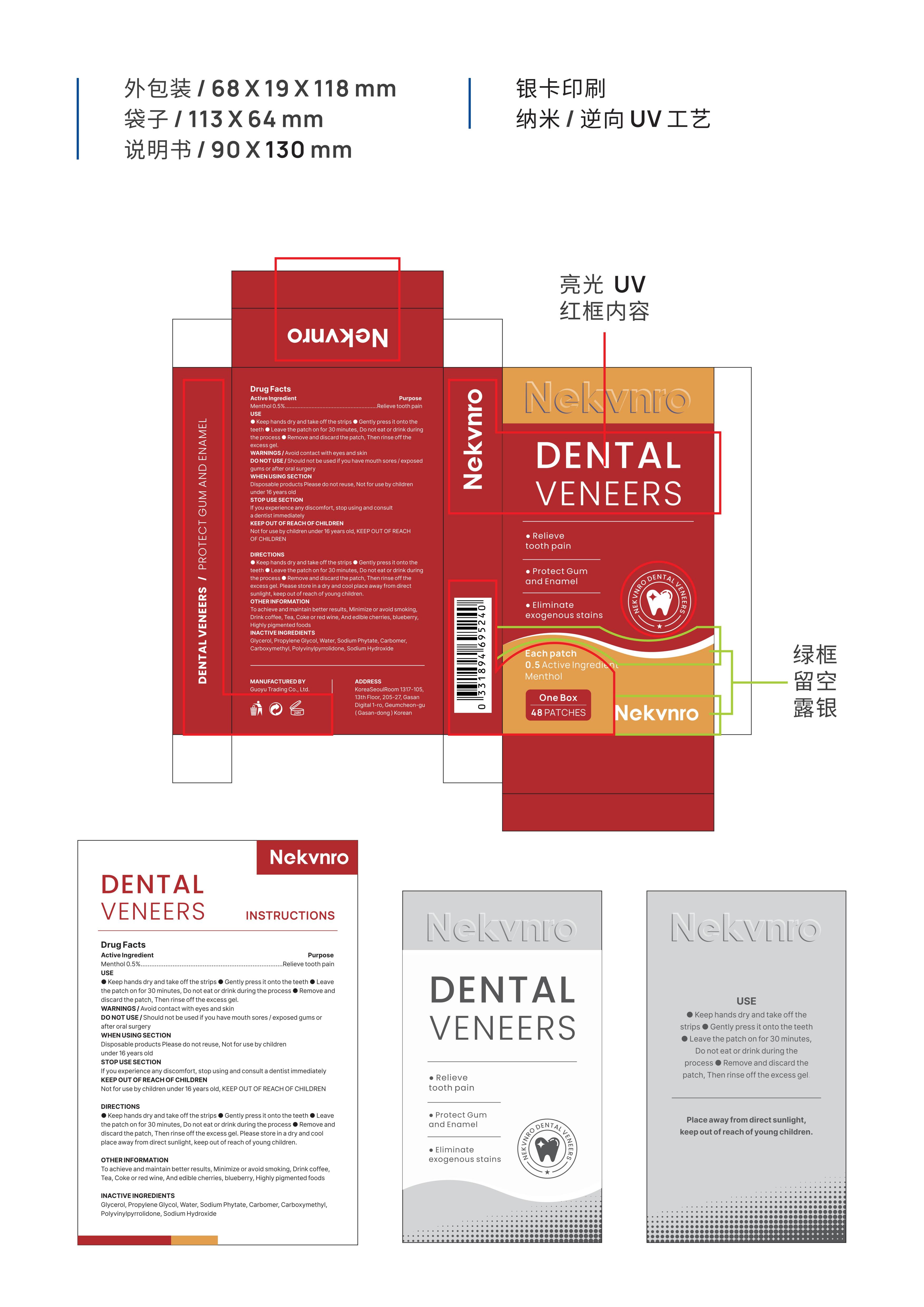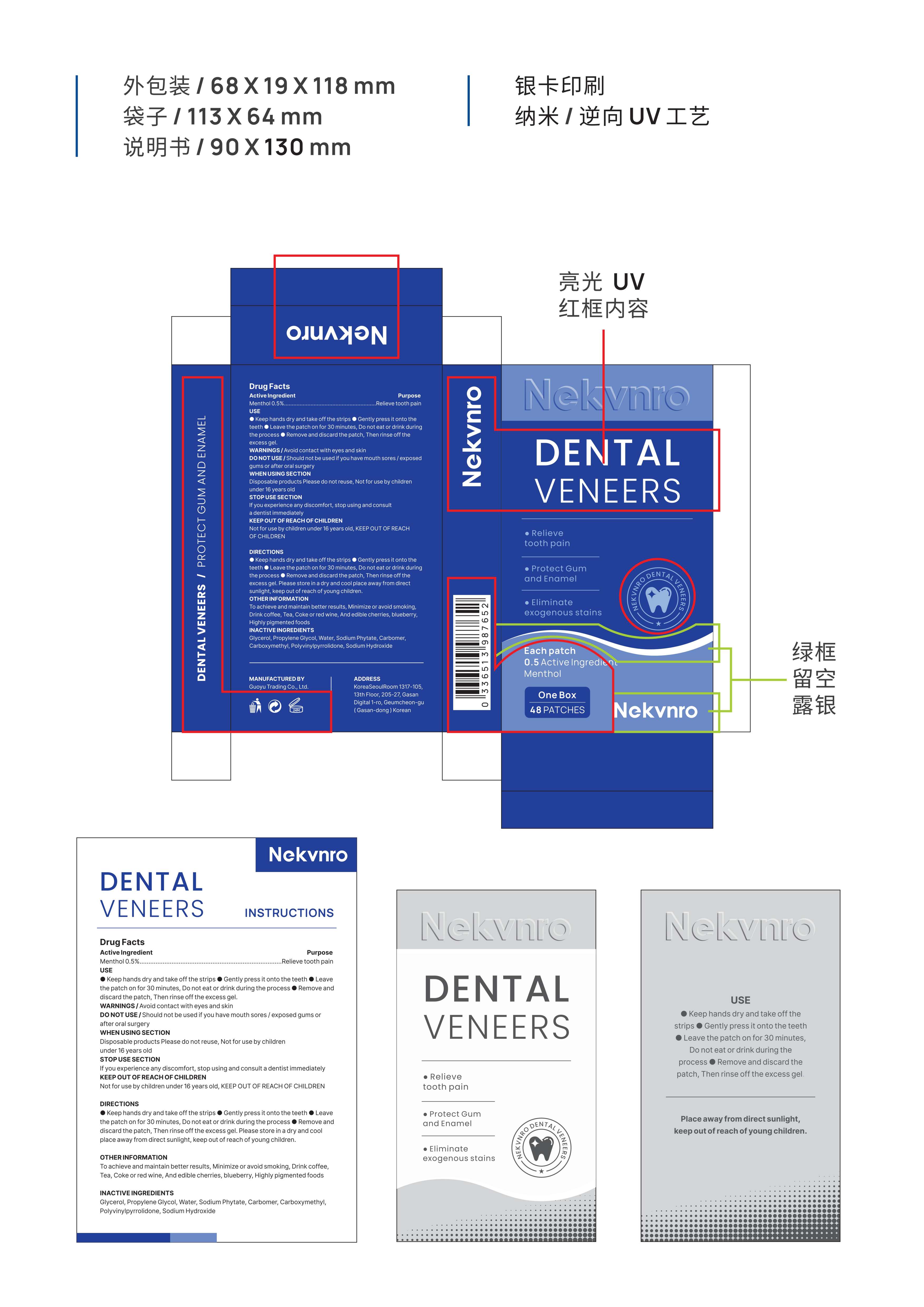 DRUG LABEL: Nekvnro Dental Veneers
NDC: 84844-006 | Form: PATCH
Manufacturer: Guoyu Trading Co., Ltd.
Category: otc | Type: HUMAN OTC DRUG LABEL
Date: 20241030

ACTIVE INGREDIENTS: MENTHOL 0.5 g/100 1
INACTIVE INGREDIENTS: CARBOMER; CARBOXYMETHYLCELLULOSE CALCIUM; GLYCERIN; PROPYLENE GLYCOL; POLYVINYL ALCOHOL (94000 MW); SODIUM HYDROXIDE; WATER; SODIUM PHYTATE

84844-006

Active Ingredient

Menthol 0.5%

Purpose

Relieve tooth pain

Use

•Keep hands dry and take off the strips

•Gently press it onto the teeth

•Leave the patch on for 30 minutes，Do not eat or drink during the process

•Remove and discard the patch，Then rinse off the excess gel.

Warnings

Avoid contact with eyes and skin

Do not use

Should not be used if you have mouth sores/exposed gums or after oral surgery

When Using

Disposable products Please do not reuse,Not for use by children under 16 years old

Stop Use

If you experience any discomfort, stop using and consult a dentist immediately

Ask Doctor

If you experience any discomfort, stop using and consult a dentist immediately

Keep Oot Of Reach Of Children

Not for use by children under 16 years old，keep out of reach of children.

Directions

•Keep hands dry and take off the strips

•Gently press it onto the teeth

•Leave the patch on for 30 minutes，Do not eat or drink during the process

•Remove and discard the patch，Then rinse off the excess gel.Please store in a dry and cool place away from direct sunlight ,keep out of reach of young children.

Other information

To achieve and maintain better results，Minimize or avoid smoking、Drink coffee、Tea、Coke or red wine，And edible cherries，blueberry，Highly pigmented foods

Inactive ingredients

Glycerol，Propylene Glycol，Water，Sodium Phytate，Carbomer，Carboxymethyl，Polyvinylpyrrolidone，Sodium Hydroxide